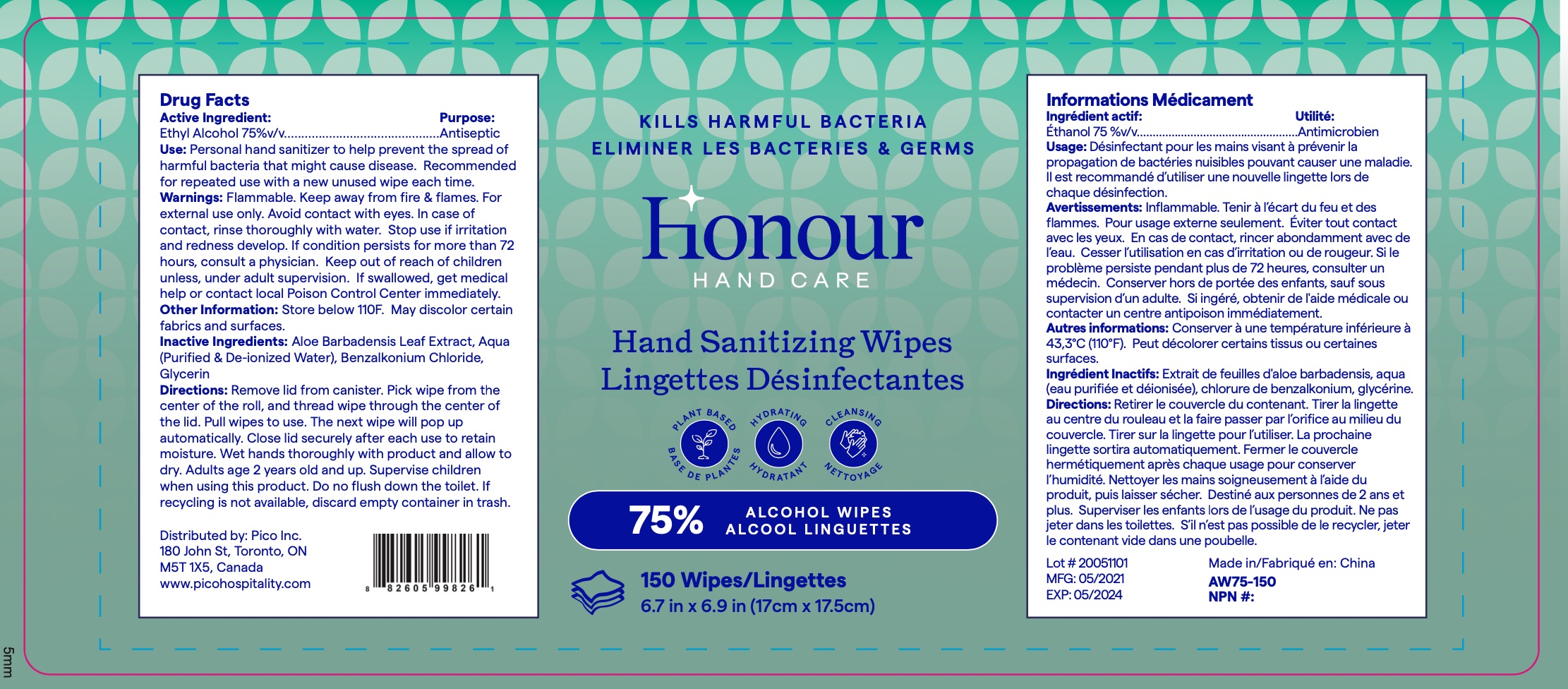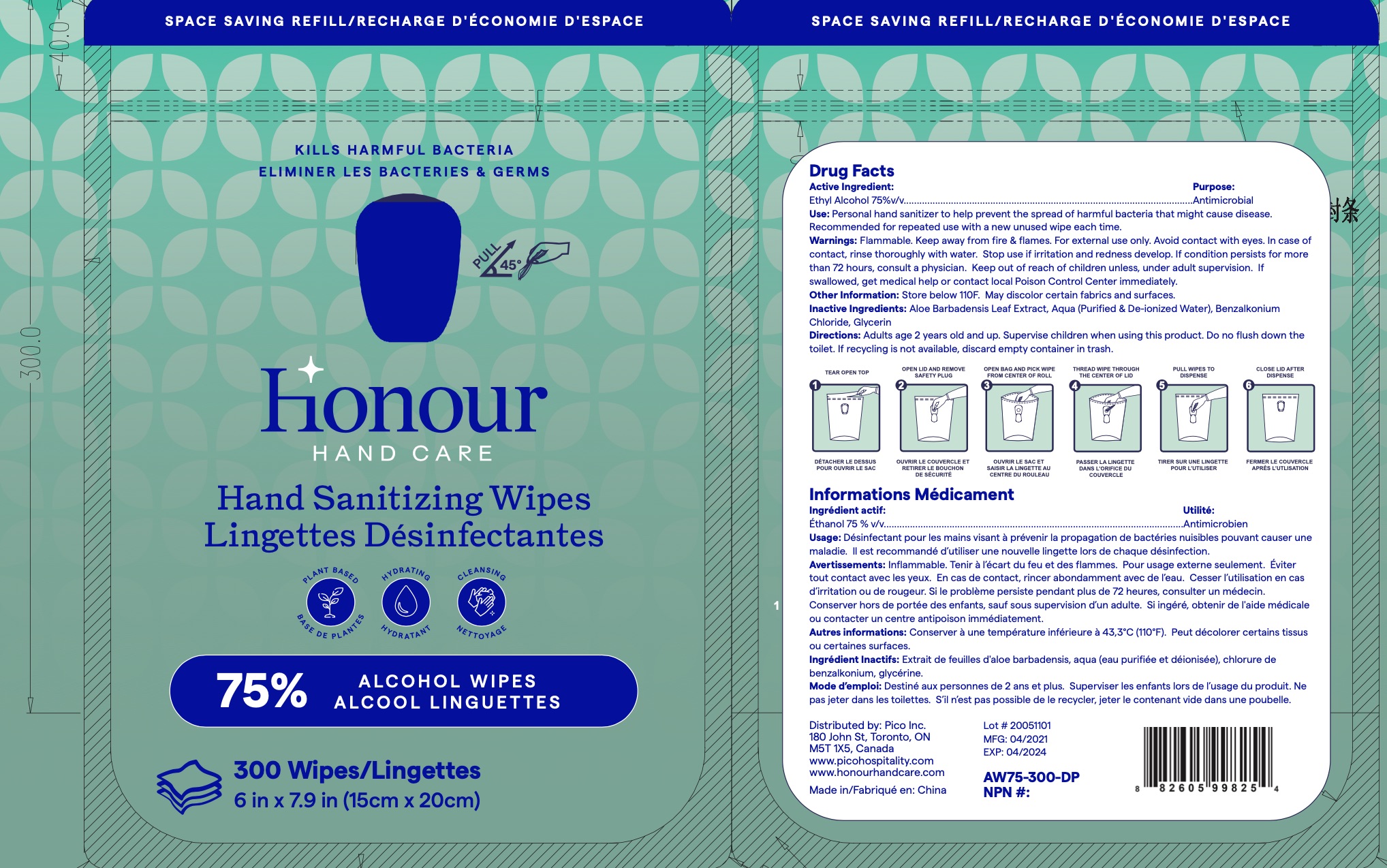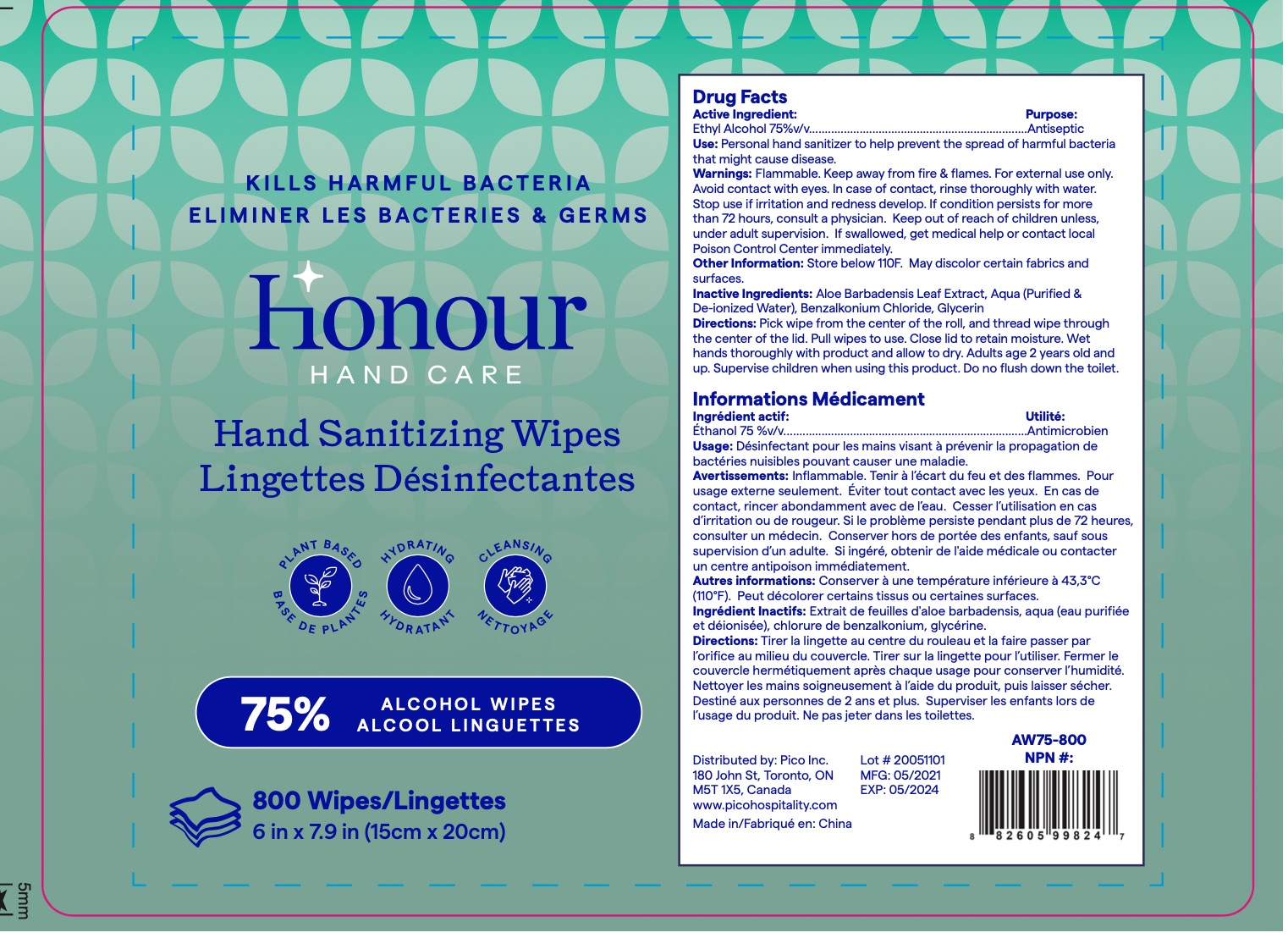 DRUG LABEL: Alcohol wipes 75% alcohol
NDC: 78082-026 | Form: CLOTH
Manufacturer: PICO INC.
Category: otc | Type: HUMAN OTC DRUG LABEL
Date: 20211217

ACTIVE INGREDIENTS: ALCOHOL 75 mL/100 1
INACTIVE INGREDIENTS: BENZALKONIUM CHLORIDE; GLYCERIN; ALOE VERA LEAF; WATER

Honour Hand Sanitizing Wipes 75% alcohol

Main Ingredients

75% alcohol

Purpose

/

INDICATIONS AND USAGE

Open the lid and the sticker, pull out the wipes needed and then press the sticker back and close the lid to avoid alcohol evaporation.

WARNINGS

Contains 75% ethanol alcohol. Keep away from heat and fire source. Place in dry and cool areas

Do not use on sensitive position, like face eye, nose and mouth

WHEN USING

1. Contains 75% ethanol alcohol. Keep away from heat and fire source. Place in dry and cool areas
2. Keep away from Children
3. Do not use on sensitive position, like face eye, nose and mouth
4. Do not flush into toilet

STOP USE

/

Keep away from Children

DOSAGE AND ADMINISTRATION

/

STORAGE AND HANDLING

/

Inactive ingredients

purified water (aqua), Aloe Leaf Extract, Glycerin, Benzalkonium chloride

Package Label - Principal Display Panel

300 wipes NDC 78082-026-01

Package 800 wipes

800 wipes NDC 78082-026-02

Package 150 wipes

150 Wipes NDC 78082-026-03